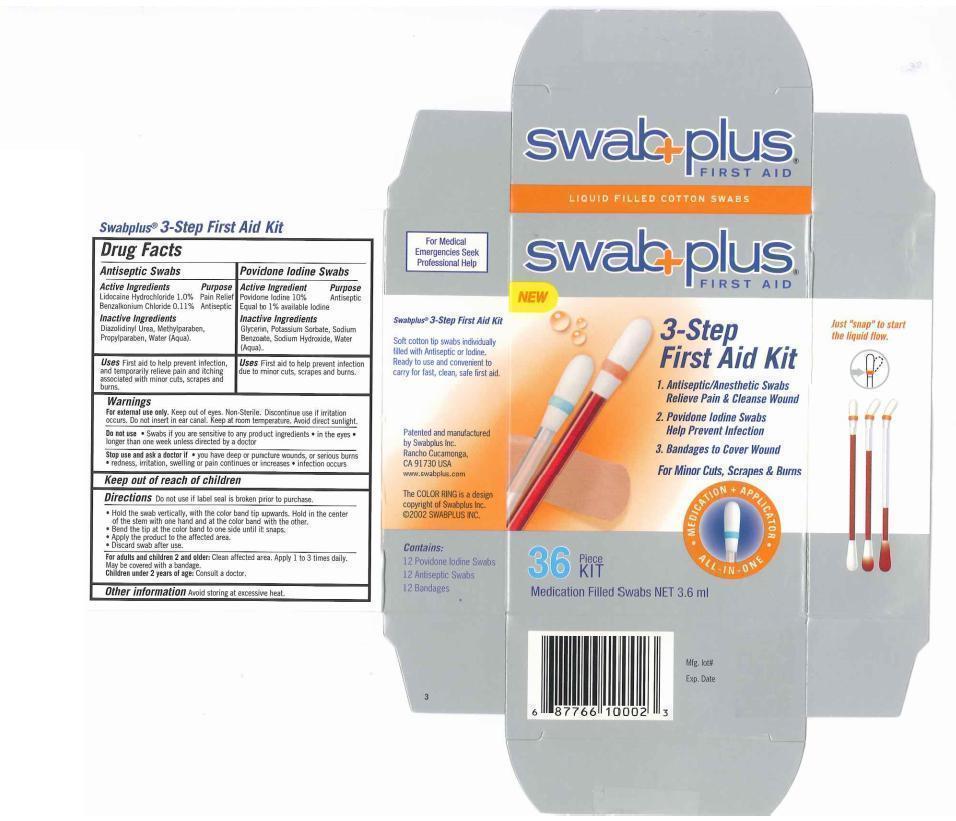 DRUG LABEL: 3-Step First Aid Kit
NDC: 65734-000 | Form: KIT | Route: TOPICAL
Manufacturer: Swabplus Inc.
Category: otc | Type: HUMAN OTC DRUG LABEL
Date: 20130318

ACTIVE INGREDIENTS: LIDOCAINE HYDROCHLORIDE 100 mg/10 mL; Benzalkonium Chloride 11 mg/10 mL; Povidone-Iodine 100 mg/10 mL
INACTIVE INGREDIENTS: Water; Diazolidinyl Urea; Methylparaben; Propylparaben; Propylene Glycol; Sodium Hydroxide; Glycerin; Water

3 Step First Aid Kit Medication Filled Swabs

Drug Facts Active Ingredients

Antiseptic Swabs

Lidocaine Hydrochloride 1.0%

Benzalkonium Chloride 0.11%

Povidone Iodine swabs:

Povidone Iodine 10%, equal to available Iodine 1% for antiseptic

Purpose

Lidocaine Hydrochloride for Pain Relief

Benzalkonium Chloride for Antiseptic

Povidone Iodine for Antiseptis

Uses

First aid to help prevent infection, and temporarily reliever pain and itching associated with minor cuts. scrapes and burn

Keep out of reach of children

Keeo out of reach of children

Directions

- Do not use if label seal is broken prior to purchase.
- Hold the swab vertically, with the color ring band tip upwards. Hold in the center of the stem with one hand and at the color band with the other.
- Bend the tip at the color band to one side until it snaps.
- Apply the product to the affected area.
- Discard swab after use.

Warnings

For external use only. Keep out of eyes. Non-Sterile. Discontinue use if irritation occurs. Do not insert inear canal. Keep at room temperture. Avoid direct sunlight.

Do not use. Swabs if you are sensitive to any product ingredients. in the eyes. longer than one week unless directed by a doctor.

Stop use and ask a doctor if you have deep or punchture wounds, or serious burns. redness, irritation, sweeling or pain continues or increases, infection occurs

Other information

For adult and children 2 and older: Clean affected area. Apply 1 to 3 times daily. May be covered with a bandage.

Children under 2 years of age: Consult a doctor.

Avoid storing at excessive heat.

Inactive Ingredients

Antiseptic swab: Dizolidinyl Urea, Methylparaben, Propylparaben, Water

Providone Iodine Swab: Glcerin, Water

Manufacturer Statement

Soft cotton tip swabs individually filled with Antiseptic or Iodine. Ready to use and convenient to carry for fast, clean, safe first aid.

Patented and manufactured by Swabplus Inc. Rancho Cucamonga, CA 91730 USA

The COLOR RING is copyrighted by Swabplus Inc. ©2007 SWABPLUS INC.

Package and label

Image of first aid carton label